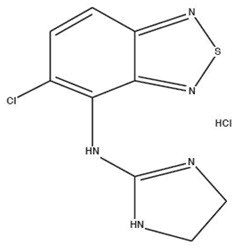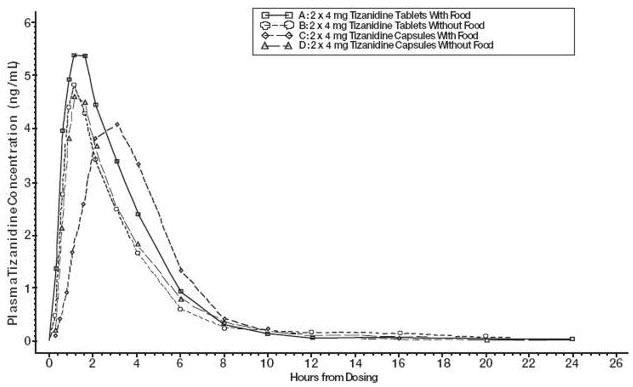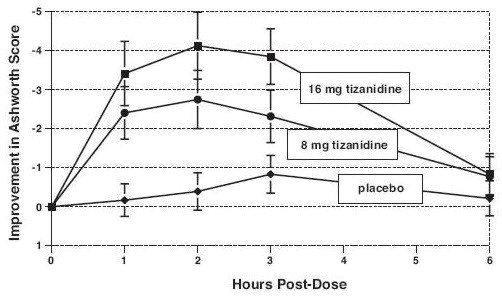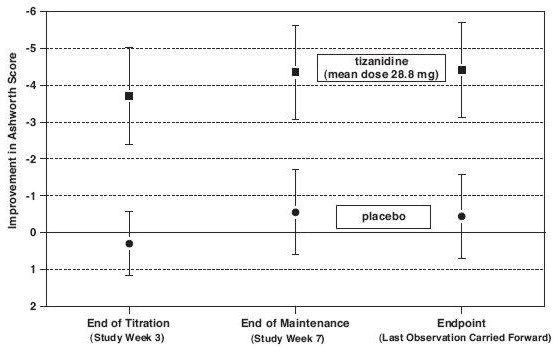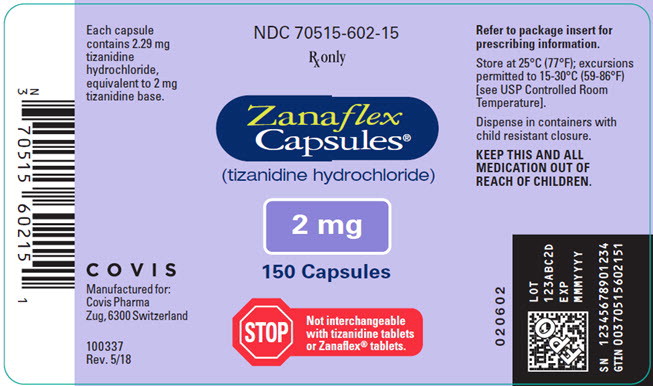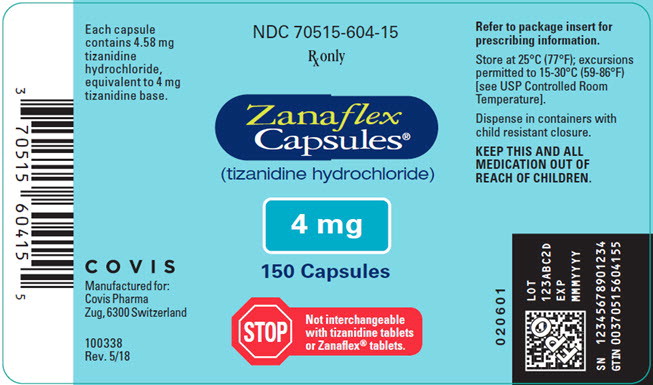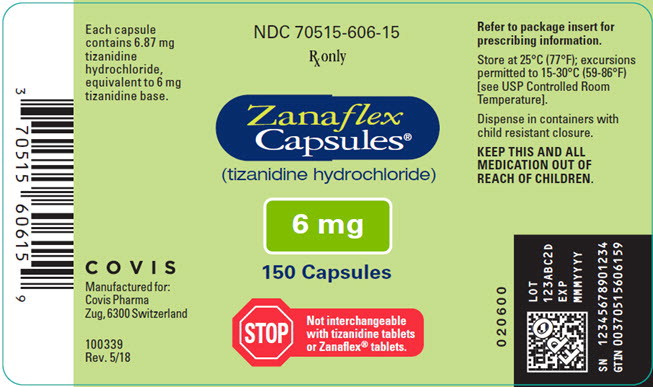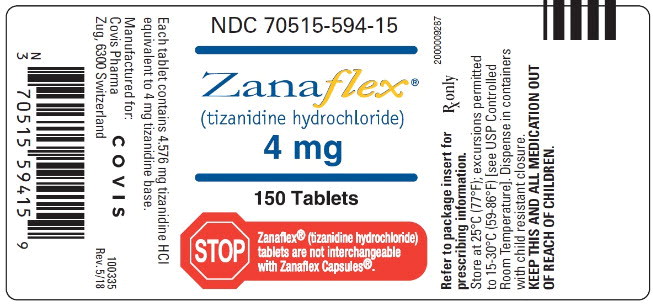 DRUG LABEL: Zanaflex
NDC: 70515-602 | Form: CAPSULE
Manufacturer: Covis Pharma US, Inc
Category: prescription | Type: HUMAN PRESCRIPTION DRUG LABEL
Date: 20250505

ACTIVE INGREDIENTS: TIZANIDINE HYDROCHLORIDE 2 mg/1 1
INACTIVE INGREDIENTS: SILICON DIOXIDE; TITANIUM DIOXIDE; GELATIN, UNSPECIFIED

HIGHLIGHTS OF PRESCRIBING INFORMATION

These highlights do not include all the information needed to use ZANAFLEX®safely and effectively. See full prescribing information for ZANAFLEX.
ZANAFLEX®(tizanidine hydrochloride) capsules, for oral use
ZANAFLEX®(tizanidine hydrochloride) tablets, for oral use
Initial U.S. Approval: 1996

1 INDICATIONS AND USAGE

Zanaflex is a central alpha-2-adrenergic agonist indicated for the management of spasticity. Because of the short duration of therapeutic effect, treatment with Zanaflex should be reserved for those daily activities and times when relief of spasticity is most important. (1)

2 DOSAGE AND ADMINISTRATION

- Recommended starting dose: 2 mg; dose can be repeated at 6 to 8 hour intervals, up to a maximum of 3 doses in 24 hours (2.1)
- Dosage can be increased by 2 mg to 4 mg per dose, with 1 to 4 days between increases; total daily dose should not exceed 36 mg (2.1)
- Tizanidine pharmacokinetics differs between tablets and capsules, and when taken with or without food. These differences could result in a change in tolerability and control of symptoms (2.1, 12.3)
- To discontinue Zanaflex, decrease dose slowly to minimize the risk of withdrawal and rebound hypertension, tachycardia, and hypertonia (2.2)

3 DOSAGE FORMS AND STRENGTHS

- Capsules: 2 mg, 4 mg or 6 mg (3)
- Tablets 4 mg (3)

4 CONTRAINDICATIONS

- Concomitant use with potent inhibitors of CYP1A2, such as fluvoxamine or ciprofloxacin (4, 5.5, 7.1, 7.2)

5 WARNINGS AND PRECAUTIONS

- Hypotension: monitor for signs and symptoms of hypotension, in particular in patients receiving concurrent antihypertensives; Zanaflex should not be used with other α2-adrenergic agonists (5.1, 7.7)
- Risk of liver injury: monitor ALTs; discontinue Zanaflex if liver injury occurs (5.2)
- Sedation: Zanaflex may interfere with everyday activities; sedative effects of Zanaflex, alcohol, and other CNS depressants are additive (5.3, 7.5, 7.6)
- Hallucinations: consider discontinuation of Zanaflex (5.4)
- Less potent inhibitors of CYP1A2: may cause hypotension, bradycardia, or excessive drowsiness, use caution if Zanaflex is used with less potent inhibitors of CYP1A2, e.g., zileuton, other fluoroquinolones, antiarrhythmics, cimetidine, famotidine, oral contraceptives, acyclovir, and ticlopidine (5.5, 7.3, 12.3)
- Renal impairment (creatinine clearance < 25 mL/min): use Zanaflex with caution, and monitor closely for dry mouth, somnolence, asthenia and dizziness as indicators of potential overdose (5.7)

6 ADVERSE REACTIONS

The most common adverse reactions (greater than 2% of 264 patients taking tizanidine and greater than in placebo-treated patients in three multiple dose, placebo-controlled studies) were dry mouth, somnolence, asthenia, dizziness, urinary tract infection, constipation, liver function tests abnormal, vomiting, speech disorder, amblyopia, urinary frequency, flu syndrome, SGPT/ALT increased, dyskinesia, nervousness, pharyngitis, and rhinitis (6.1)

To report SUSPECTED ADVERSE REACTIONS, contact Covis Pharma at 1-866-488-4423 or FDA at 1-800-FDA-1088 or www.fda.gov/medwatch.

8 USE IN SPECIFIC POPULATIONS

- Pregnancy: Based on animal data, may cause fetal harm (8.1)
- Geriatric use: Zanaflex should be used with caution in elderly patients because clearance is decreased four-fold (8.5)

FULL PRESCRIBING INFORMATION

1 INDICATIONS AND USAGE

Zanaflex is indicated for the management of spasticity. Because of the short duration of therapeutic effect, treatment with Zanaflex should be reserved for those daily activities and times when relief of spasticity is most important [see Dosage and Administration (2.1)] .

2 DOSAGE AND ADMINISTRATION

2.1 Dosing Information

Zanaflex Capsules®or Zanaflex®tablets may be prescribed with or without food. Once the formulation has been selected and the decision to take with or without food has been made, this regimen should not be altered.

Food has complex effects on tizanidine pharmacokinetics, which differ with the different formulations. Zanaflex Capsules and Zanaflex tablets are bioequivalent to each other under fasting conditions (more than 3 hours after a meal), but not under fed conditions (within 30 minutes of a meal). These pharmacokinetic differences may result in clinically significant differences when switching administration of tablet and capsules and when switching administration between the fed or fasted state. These changes may result in increased adverse events, or delayed or more rapid onset of activity, depending upon the nature of the switch. For this reason, the prescriber should be thoroughly familiar with the changes in kinetics associated with these different conditions [see Clinical Pharmacology (12.3)] .

The recommended starting dose is 2 mg. Because the effect of Zanaflex peaks at approximately 1 to 2 hours post-dose and dissipates between 3 to 6 hours post-dose, treatment can be repeated at 6 to 8 hour intervals, as needed, to a maximum of three doses in 24 hours.

Dosage can be gradually increased by 2 mg to 4 mg at each dose, with 1 to 4 days between dosage increases, until a satisfactory reduction of muscle tone is achieved. The total daily dose should not exceed 36 mg. Single doses greater than 16 mg have not been studied.

2.2 Dosing in Patients with Renal Impairment

Zanaflex should be used with caution in patients with renal insufficiency (creatinine clearance < 25 mL/min), as clearance is reduced by more than 50%. In these patients, during titration, the individual doses should be reduced. If higher doses are required, individual doses rather than dosing frequency should be increased [see Warnings and Precautions (5.7)] .

2.3 Dosing in Patients with Hepatic Impairment

Zanaflex should be used with caution in patients with any hepatic impairment. In these patients, during titration, the individual doses should be reduced. If higher doses are required, individual doses rather than dosing frequency should be increased. Monitoring of aminotransferase levels is recommended for baseline and 1 month after maximum dose is achieved, or if hepatic injury is suspected [see Use in Specific Populations (8.7)] .

2.4 Drug Discontinuation

If therapy needs to be discontinued, particularly in patients who have been receiving high doses (20 mg to 36 mg daily) for long periods (9 weeks or more) or who may be on concomitant treatment with narcotics, the dose should be decreased slowly (2 mg to 4 mg per day) to minimize the risk of withdrawal and rebound hypertension, tachycardia, and hypertonia [see Drug Abuse and Dependence (9.3)] .

3 DOSAGE FORMS AND STRENGTHS

Capsules

2 mg: Light blue opaque body with a light blue opaque cap with “2 MG” printed on the cap

4 mg: White opaque body with a blue opaque cap with “4 MG” printed on the cap

6 mg: Blue opaque body with a white stripe and blue opaque cap with “6 MG” printed on the cap

Tablets

4 mg white, uncoated tablets with a quadrisecting score on one side and debossed with “A594” on the other side

4 CONTRAINDICATIONS

Zanaflex is contraindicated in patients taking potent inhibitors of CYP1A2, such as fluvoxamine or ciprofloxacin [see Drug Interactions (7.1, 7.2)] .

5 WARNINGS AND PRECAUTIONS

5.1 Hypotension

Tizanidine is an α2-adrenergic agonist that can produce hypotension. Syncope has been reported in the post marketing setting. The chance of significant hypotension may possibly be minimized by titration of the dose and by focusing attention on signs and symptoms of hypotension prior to dose advancement. In addition, patients moving from a supine to fixed upright position may be at increased risk for hypotension and orthostatic effects.

Monitor for hypotension when Zanaflex is used in patients receiving concurrent antihypertensive therapy. It is not recommended that Zanaflex be used with other α2-adrenergic agonists. Clinically significant hypotension (decreases in both systolic and diastolic pressure) has been reported with concomitant administration of either fluvoxamine or ciprofloxacin and single doses of 4 mg of Zanaflex. Therefore, concomitant use of Zanaflex with fluvoxamine or with ciprofloxacin, potent inhibitors of CYP1A2, is contraindicated [see Contraindications (4) and Drug Interactions (7.1, 7.2)] .

5.2 Risk of Liver Injury

Zanaflex may cause hepatocellular liver injury. Zanaflex should be used with caution in patients with any hepatic impairment. Monitoring of aminotransferase levels is recommended for baseline and 1 month after maximum dose is achieved, or if hepatic injury is suspected [see Dosage and Administration (2.3) and Use in Specific Populations (8.7)] .

5.3 Sedation

Zanaflex can cause sedation, which may interfere with everyday activity. In the multiple dose studies, the prevalence of patients with sedation peaked following the first week of titration and then remained stable for the duration of the maintenance phase of the study. The CNS depressant effects of Zanaflex with alcohol and other CNS depressants (e.g., benzodiazepines, opioids, tricyclic antidepressants) may be additive. Monitor patients who take Zanaflex with another CNS depressant for symptoms of excess sedation [see Drug Interactions (7.5, 7.6)] .

5.4 Hallucinosis/Psychotic-Like Symptoms

Zanaflex use has been associated with hallucinations. Formed, visual hallucinations or delusions have been reported in 5 of 170 patients (3%) in two North American controlled clinical studies. Most of the patients were aware that the events were unreal. One patient developed psychosis in association with the hallucinations. One patient among these 5 continued to have problems for at least 2 weeks following discontinuation of tizanidine. Consider discontinuing Zanaflex in patients who develop hallucinations.

5.5 Interaction with CYP1A2 Inhibitors

Because of potential drug interactions, Zanaflex is contraindicated in patients taking potent CYP1A2 inhibitors, such as fluvoxamine or ciprofloxacin. Adverse reactions such as hypotension, bradycardia, or excessive drowsiness can occur when Zanaflex is taken with other CYP1A2 inhibitors, such as zileuton, fluoroquinolones other than ciprofloxacin (which is contraindicated), antiarrhythmics (amiodarone, mexiletine, propafenone), cimetidine, famotidine, oral contraceptives, acyclovir, and ticlopidine). Concomitant use should be avoided unless the necessity for Zanaflex therapy is clinically evident. In such a case, use with caution [see Drug Interactions (7.3) and Clinical Pharmacology (12.3)] .

5.6 Hypersensitivity Reactions

Zanaflex can cause anaphylaxis. Signs and symptoms including respiratory compromise, urticaria, and angioedema of the throat and tongue have been reported. Patients should be informed of the signs and symptoms of severe allergic reactions and instructed to discontinue Zanaflex and seek immediate medical care should these signs and symptoms occur [see Contraindications (4)] .

5.7 Increased Risk of Adverse Reactions in Patients with Renal Impairment

Zanaflex should be used with caution in patients with renal insufficiency (creatinine clearance < 25 mL/min), as clearance is reduced by more than 50%. In these patients, during titration, the individual doses should be reduced. If higher doses are required, individual doses rather than dosing frequency should be increased. These patients should be monitored closely for the onset or increase in severity of the common adverse events (dry mouth, somnolence, asthenia and dizziness) as indicators of potential overdose [see Dosage and Administration (2.2) and Use in Specific Populations (8.6)] .

5.8 Withdrawal Adverse Reactions

Withdrawal adverse reactions include rebound hypertension, tachycardia, and hypertonia. To minimize the risk of these reactions, particularly in patients who have been receiving high doses (20 to 28 mg daily) for long periods of time (9 weeks or more) or who may be on concomitant treatment with narcotics, the dose should be decreased slowly (2 to 4 mg per day) [see Dosage and Administration (2.2)] .

6 ADVERSE REACTIONS

The following adverse reactions are described elsewhere in other sections of the prescribing information:

- Hypotension [see Warnings and Precautions (5.1)]
- Liver Injury [see Warnings and Precautions (5.2)]
- Sedation [see Warnings and Precautions (5.3)]
- Hallucinosis/Psychotic-Like Symptoms [see Warnings and Precautions (5.4)]
- Hypersensitivity Reactions [see Warnings and Precautions (5.6)]

6.1 Clinical Trials Experience

Because clinical studies are conducted under widely varying conditions, adverse reaction rates observed in the clinical studies of a drug cannot be directly compared to rates in the clinical studies of another drug and may not reflect the rates observed in clinical practice.

Three double-blind, randomized, placebo-controlled clinical studies were conducted to evaluate the effect of tizanidine on spasticity control. Two studies were conducted in patients with multiple sclerosis and one in patients with spinal cord injury. Each study had a 13-week active treatment period which included a 3-week titration phase to the maximum tolerated dose up to 36 mg/day in three divided doses, a 9-week plateau phase where the dose of tizanidine was held constant and a 1-week dose tapering. In all, 264 patients received tizanidine and 261 patients received placebo. Across the three studies patient ages ranged from 15–69 years and 51.4 percent were women. The median dose during the plateau phase ranged from 20–28 mg/day.

The most frequent adverse reactions reported in multiple dose, placebo-controlled clinical studies involving 264 patients with spasticity were dry mouth, somnolence/sedation, asthenia (weakness, fatigue and/or tiredness) and dizziness. Three-quarters of the patients rated the events as mild to moderate and one-quarter of the patients rated the events as being severe. These events appeared to be dose related.

Table 1lists signs and symptoms that were reported in greater than 2% of patients in three multiple dose, placebo-controlled studies who received Zanaflex where the frequency in the Zanaflex group was greater than the placebo group. For comparison purposes, the corresponding frequency of the event (per 100 patients) among placebo treated patients is also provided.

Table 1: Multiple Dose, Placebo-Controlled Studies - Frequent (>2%) Adverse Reactions Reported for Which Zanaflex Tablets Incidence is Greater than Placebo
Event | Placebo N = 261 % | Zanaflex Tablet N = 264 %
Dry mouth | 10 | 49
Somnolence | 10 | 48
Asthenia [(weakness, fatigue, and/or tiredness)] | 16 | 41
Dizziness | 4 | 16
UTI | 7 | 10
Infection | 5 | 6
Constipation | 1 | 4
Liver test abnormality | 2 | 6
Vomiting | 0 | 3
Speech disorder | 0 | 3
Amblyopia (blurred vision) | <1 | 3
Urinary frequency | 2 | 3
Flu syndrome | 2 | 3
Dyskinesia | 0 | 3
Nervousness | <1 | 3
Pharyngitis | 1 | 3
Rhinitis | 2 | 3

In the single dose, placebo-controlled study involving 142 patients with spasticity due to multiple sclerosis (Study 1) [see Clinical Studies (14)] , the patients were specifically asked if they had experienced any of the four most common adverse reactions: dry mouth, somnolence (drowsiness), asthenia (weakness, fatigue and/or tiredness) and dizziness. In addition, hypotension and bradycardia were observed. The occurrence of these reactions is summarized in Table 2. Other events were, in general, reported at a rate of 2% or less.

Table 2: Single Dose, Placebo-Controlled Study - Common Adverse Reactions Reported
Event | Placebo N = 48 % | Zanaflex Tablet, 8mg, N = 45 % | Zanaflex Tablet, 16 mg, N = 49 %
Somnolence | 31 | 78 | 92
Dry mouth | 35 | 76 | 88
Asthenia [(weakness, fatigue, and/or tiredness)] | 40 | 67 | 78
Dizziness | 4 | 22 | 45
Hypotension | 0 | 16 | 33
Bradycardia | 0 | 2 | 10

6.2 Postmarketing Experience

The following adverse reactions have been identified during post approval use of Zanaflex. Because these reactions are reported voluntarily from a population of uncertain size, it is not always possible to reliably estimate their frequency or establish a causal relationship to drug exposure.

Certain events, such as somnolence, dry mouth, hypotension, decreased blood pressure, bradycardia, dizziness, weakness or asthenia, muscle spasms, hallucinations, fatigue, liver function test abnormality and hepatotoxicity, have been observed in post marketing and clinical trials and are discussed in previous sections of this document.

The following adverse reactions have been identified as occurring in the post marketing experience of Zanaflex. Based on the information provided regarding these reactions, a causal relationship with Zanaflex cannot be entirely excluded. The events are listed in order of decreasing clinical significance; severity in the post marketing setting is not reported.

- Stevens Johnson Syndrome
- Anaphylactic Reaction
- Exfoliative Dermatitis
- Ventricular Tachycardia
- Hepatitis
- Convulsion
- Depression
- Arthralgia
- Paresthesia
- Rash
- Tremor

7 DRUG INTERACTIONS

7.1 Fluvoxamine

Concomitant use of fluvoxamine and Zanaflex is contraindicated. Changes in pharmacokinetics of tizanidine when administered with fluvoxamine resulted in significantly decreased blood pressure, increased drowsiness, and increased psychomotor impairment [see Contraindications (4) and Clinical Pharmacology (12.3)] .

7.2 Ciprofloxacin

Concomitant use of ciprofloxacin and Zanaflex is contraindicated. Changes in pharmacokinetics of tizanidine when administered with ciprofloxacin resulted in significantly decreased blood pressure, increased drowsiness, and increased psychomotor impairment [see Contraindications (4) and Clinical Pharmacology (12.3)] .

7.3 CYP1A2 Inhibitors other than Fluvoxamine and Ciprofloxacin

Because of potential drug interactions, concomitant use of Zanaflex with other CYP1A2 inhibitors, such as zileuton, fluoroquinolones other than strong CYP1A2 inhibitors (which are contraindicated), antiarrhythmics (amiodarone, mexiletine, propafenone, and verapamil), cimetidine, famotidine, oral contraceptives, acyclovir, and ticlopidine) should be avoided. If their use is clinically necessary, therapy should be initiated with 2 mg dose and increased in 2–4 mg steps daily based on patient response to therapy. If adverse reactions such as hypotension, bradycardia, or excessive drowsiness occur, reduce or discontinue Zanaflex therapy [see Warnings and Precautions (5.5) and Clinical Pharmacology (12.3)] .

7.4 Oral Contraceptives

Concomitant use of Zanaflex with oral contraceptives is not recommended. However, if concomitant use is clinically necessary, initiate Zanaflex with a single 2 mg dose and increase in 2–4 mg steps daily based on patient response to therapy. If adverse reactions such as hypotension, bradycardia, or excessive drowsiness occur, reduce or discontinue Zanaflex therapy [see Clinical Pharmacology (12.3)] .

7.5 Alcohol

Alcohol increases the overall amount of drug in the bloodstream after a dose of Zanaflex. This was associated with an increase in adverse reactions of Zanaflex. The CNS depressant effects of Zanaflex and alcohol are additive [see Clinical Pharmacology (12.3)] .

7.6 Other CNS Depressants

The sedative effects of Zanaflex with CNS depressants (e.g., benzodiazepines, opioids, tricyclic antidepressants) may be additive. Monitor patients who take Zanaflex with another CNS depressant for symptoms of excess sedation [see Clinical Pharmacology (12.3)] .

7.7 α2-Adrenergic Agonists

Because hypotensive effects may be cumulative, it is not recommended that Zanaflex be used with other α2-adrenergic agonists [see Warnings and Precautions (5.1)] .

8 USE IN SPECIFIC POPULATIONS

8.1 Pregnancy

Risk Summary

There are no adequate data on the developmental risk associated with use of Zanaflex in pregnant women. In animal studies, administration of tizanidine during pregnancy resulted in developmental toxicity (embryofetal and postnatal offspring mortality and growth deficits) at doses less than those used clinically, which were not associated with maternal toxicity (see Animal Data).

In the U.S. general population, the estimated background risk of major birth defects and miscarriage in clinically recognized pregnancies is 2% - 4% and 15% - 20%, respectively. The background risk of major birth defects and miscarriage for the indicated population is unknown.

Data

Animal Data

Oral administration of tizanidine (0.3 to 100 mg/kg/day) to pregnant rats during the period of organogenesis resulted in embryofetal and postnatal offspring mortality and reductions in body weight at doses of 30 mg/kg/day and above. Maternal toxicity was observed at the highest dose tested. The no-effect dose for embryofetal developmental toxicity in rats (3 mg/kg/day) is similar to the maximum recommended human dose (MRHD) of 36 mg/day on a body surface area (mg/m^2) basis.

Oral administration of tizanidine (1 to 100 mg/kg/day) to pregnant rabbits during the period of organogenesis resulted in embryofetal and postnatal offspring mortality at all doses. Maternal toxicity was observed at the highest dose tested. Oral administration of tizanidine (10 and 30 mg/kg/day) during the perinatal period of pregnancy (2-6 days prior to delivery) resulted in increased postnatal offspring mortality at both doses. A no-effect dose for embryofetal developmental toxicity in rabbit was not identified. The lowest dose tested (1 mg/kg/day) is less than the MRHD on a mg/m^2basis.

In a pre- and postnatal development study in rats, oral administration of tizanidine (3 to 30 mg/kg/day) resulted in increased postnatal offspring mortality. A no-effect dose for pre- and postnatal developmental toxicity was not identified. The lowest dose tested (3 mg/kg/day) is similar to the MRHD on a mg/m^2basis, respectively.

8.2 Lactation

Risk Summary

There are no data on the presence of tizanidine in human milk, the effects on the breastfed infant, or the effects on human milk production. Animal studies have reported the presence of tizanidine in the milk of lactating animals.

The developmental and health benefits of breastfeeding should be considered along with the mother’s clinical need for Zanaflex and any potential adverse effects on the breastfed infant from Zanaflex or from the underlying maternal condition.

8.3 Females and Males of Reproductive Potential

There are no adequate and well-controlled studies in humans on the effect of Zanaflex on female or male reproductive potential. Oral administration of tizanidine to male and female rats resulted in adverse effects on fertility [see Nonclinical Toxicology (13.1)].

8.4 Pediatric Use

Safety and effectiveness in pediatric patients have not been established.

8.5 Geriatric Use

Zanaflex is known to be substantially excreted by the kidney, and the risk of adverse reactions to this drug may be greater in patients with impaired renal function. Because elderly patients are more likely to have decreased renal function, care should be taken in dose selection, and it may be useful to monitor renal function.

Clinical studies of Zanaflex did not include sufficient numbers of subjects aged 65 and over to determine whether they respond differently than younger subjects. Cross-study comparison of pharmacokinetic data following single dose administration of 6 mg Zanaflex showed that younger subjects cleared the drug four times faster than the elderly subjects. In elderly patients with renal insufficiency (creatinine clearance < 25 mL/min), tizanidine clearance is reduced by more than 50% compared to healthy elderly subjects; this would be expected to lead to a longer duration of clinical effect. During titration, the individual doses should be reduced. If higher doses are required, individual doses rather than dosing frequency should be increased. Monitor elderly patients because they may have an increased risk for adverse reactions associated with Zanaflex.

8.6 Impaired Renal Function

Zanaflex is known to be substantially excreted by the kidney, and the risk of adverse reactions to this drug may be greater in patients with impaired renal function. In patients with renal insufficiency (creatinine clearance < 25 mL/min), clearance was reduced by more than 50%. In these patients, individual doses should be reduced during titration. If higher doses are required, individual doses rather than dosing frequency should be increased. These patients should be monitored closely for the onset or increase in severity of Zanaflex common adverse events (dry mouth, somnolence, asthenia and dizziness) as indicators of potential overdosage [see Dosage and Administration (2.2), Warnings and Precautions (5.7) and Clinical Pharmacology (12.3)] .

8.7 Impaired Hepatic Function

The influence of hepatic impairment on the pharmacokinetics of tizanidine has not been evaluated. Because tizanidine is extensively metabolized in the liver, hepatic impairment would be expected to have significant effects on pharmacokinetics of tizanidine. [see Dosing and Administration (2.3), Warnings and Precautions (5.2), and Clinical Pharmacology (12.3)] .

9 DRUG ABUSE AND DEPENDENCE

9.2 Abuse

Abuse potential was not evaluated in human studies. Rats were able to distinguish tizanidine from saline in a standard discrimination paradigm, after training, but failed to generalize the effects of morphine, cocaine, diazepam, or phenobarbital to tizanidine.

9.3 Dependence

Tizanidine is closely related to clonidine, which is often abused in combination with narcotics and is known to cause symptoms of rebound upon abrupt withdrawal. Three cases of rebound symptoms on sudden withdrawal of tizanidine have been reported. The case reports suggest that these patients were also misusing narcotics. Withdrawal symptoms included hypertension, tachycardia, hypertonia, tremor, and anxiety. Withdrawal symptoms are more likely to occur in cases where high doses are used, especially for prolonged periods, or with concomitant use of narcotics. If therapy needs to be discontinued, the dose should be decreased slowly to minimize the risk of withdrawal symptoms [see Dosage and Administration (2.2)] .

Monkeys were shown to self-administer tizanidine in a dose-dependent manner, and abrupt cessation of tizanidine produced transient signs of withdrawal at doses > 35 times the maximum recommended human dose on a mg/m^2basis. These transient withdrawal signs (increased locomotion, body twitching, and aversive behavior toward the observer) were not reversed by naloxone administration.

10 OVERDOSAGE

A review of the safety surveillance database revealed cases of intentional and accidental Zanaflex overdose. Some of the cases resulted in fatality and many of the intentional overdoses were with multiple drugs including CNS depressants. The clinical manifestations of tizanidine overdose were consistent with its known pharmacology. In the majority of cases a decrease in sensorium was observed including lethargy, somnolence, confusion and coma. Depressed cardiac function is also observed including most often bradycardia and hypotension. Respiratory depression is another common feature of tizanidine overdose.

Should overdose occur, basic steps to ensure the adequacy of an airway and the monitoring of cardiovascular and respiratory systems should be undertaken. Tizanidine is a lipid-soluble drug, which is only slightly soluble in water and methanol. Therefore, dialysis is not likely to be an efficient method of removing drug from the body. In general, symptoms resolve within one to three days following discontinuation of tizanidine and administration of appropriate therapy. Due to the similar mechanism of action, symptoms and management of tizanidine overdose are similar to that following clonidine overdose. For the most recent information concerning the management of overdose, contact a poison control center.

11 DESCRIPTION

Zanaflex®(tizanidine hydrochloride) is a central alpha2-adrenergic agonist. Tizanidine HCl is a white to off-white, fine crystalline powder, which is odorless or with a faint characteristic odor. Tizanidine is slightly soluble in water and methanol; solubility in water decreases as the pH increases. Its chemical name is 5-chloro-4-(2-imidazolin-2-ylamino)-2,1,3-benzothiadiazole monohydrochloride. Tizanidine’s molecular formula is C9H8ClN5S-HCl, its molecular weight is 290.2 and its structural formula is:

Zanaflex Capsules®are supplied as 2, 4, and 6 mg capsules for oral administration. Zanaflex Capsules®contain the active ingredient, tizanidine hydrochloride (2.29 mg equivalent to 2 mg tizanidine base, 4.58 mg equivalent to 4 mg tizanidine base, and 6.87 mg equivalent to 6 mg tizanidine base), and the inactive ingredients, hypromellose, silicon dioxide, sugar spheres, titanium dioxide, gelatin, and colorants.

Zanaflex®tablets are supplied as 4 mg tablets for oral administration. Zanaflex®tablets contain the active ingredient, tizanidine hydrochloride (4.58 mg equivalent to 4 mg tizanidine base), and the inactive ingredients, colloidal silicon dioxide, stearic acid, microcrystalline cellulose and anhydrous lactose.

12 CLINICAL PHARMACOLOGY

12.1 Mechanism of Action

Tizanidine is a central alpha-2-adrenergic receptor agonist and presumably reduces spasticity by increasing presynaptic inhibition of motor neurons. The effects of tizanidine are greatest on polysynaptic pathways. The overall effect of these actions is thought to reduce facilitation of spinal motor neurons.

12.3 Pharmacokinetics

Absorption and Distribution

Following oral administration, tizanidine is essentially completely absorbed. The absolute oral bioavailability of tizanidine is approximately 40% (CV = 24%), due to extensive first-pass hepatic metabolism. Tizanidine is extensively distributed throughout the body with a mean steady state volume of distribution of 2.4 L/kg (CV = 21%) following intravenous administration in healthy adult volunteers. Tizanidine is approximately 30% bound to plasma proteins.

Differences Between Zanaflex Capsules® and Zanaflex® Tablets

Zanaflex Capsules®and Zanaflex®tablets are bioequivalent to each other under fasting conditions, but not under fed conditions. A single dose of either two 4 mg tablets or two 4 mg capsules was administered under fed and fasting conditions in an open label, four period, randomized crossover study in 96 human volunteers, of whom 81 were eligible for the statistical analysis. Following oral administration of either the tablet or capsule (in the fasted state), peak plasma concentrations of tizanidine occurred 1.0 hours after dosing with a half-life of approximately 2 hours. When two 4 mg tablets were administered with food, the mean maximal plasma concentration was increased by approximately 30%, and the median time to peak plasma concentration was increased by 25 minutes, to 1 hour and 25 minutes. In contrast, when two 4 mg capsules were administered with food, the mean maximal plasma concentration was decreased by 20%, the median time to peak plasma concentration was increased 2 to 3 hours. Consequently, the mean Cmaxfor the capsule when administered with food is approximately 66% the Cmaxfor the tablet when administered with food.

Food also increased the extent of absorption for both the tablets and capsules. The increase with the tablet (~30%) was significantly greater than with the capsule (~10%). Consequently, when each was administered with food, the amount absorbed from the capsule was about 80% of the amount absorbed from the tablet. Administration of the capsule contents sprinkled on applesauce was not bioequivalent to administration of an intact capsule under fasting conditions. Administration of the capsule contents on applesauce resulted in a 15%–20% increase in Cmaxand AUC of tizanidine and a 15 minute decrease in the median lag time and time to peak concentration compared to administration of an intact capsule while fasting.

Metabolism and Excretion

Tizanidine has linear pharmacokinetics over the doses studied in clinical development (1–20 mg). Tizanidine has a half-life of approximately 2.5 hours (CV=33%). Approximately 95% of an administered dose is metabolized. The primary cytochrome P450 isoenzyme involved in tizanidine metabolism is CYP1A2. Tizanidine metabolites are not known to be active; their half-lives range from 20 to 40 hours.

Following single and multiple oral dosing of^14C-tizanidine, an average of 60% and 20% of total radioactivity was recovered in the urine and feces, respectively.

Specific Populations

Age Effects

No specific pharmacokinetic study was conducted to investigate age effects. Cross study comparison of pharmacokinetic data following single dose administration of 6 mg Zanaflex showed that younger subjects cleared the drug four times faster than the elderly subjects. Zanaflex has not been evaluated in children [see Use in Specific Populations (8.4, 8.5)] .

Hepatic Impairment

The influence of hepatic impairment on the pharmacokinetics of tizanidine has not been evaluated. Because tizanidine is extensively metabolized in the liver, hepatic impairment would be expected to have significant effects on pharmacokinetics of tizanidine. Zanaflex is not recommended in this patient population [see Use in Specific Populations (8.7)] .

Renal Impairment

Tizanidine clearance is reduced by more than 50% in elderly patients with renal insufficiency (creatinine clearance < 25 mL/min) compared to healthy elderly subjects; this would be expected to lead to a longer duration of clinical effect. Zanaflex should be used with caution in renally impaired patients [see Warnings and Precautions (5.7) and Use in Specific Populations (8.6)] .

Gender Effects

No specific pharmacokinetic study was conducted to investigate gender effects. Retrospective analysis of pharmacokinetic data, however, following single and multiple dose administration of 4 mg Zanaflex showed that gender had no effect on the pharmacokinetics of tizanidine.

Race Effects

Pharmacokinetic differences due to race have not been studied.

Drug Interactions

CYP1A2 Inhibitors

The interaction between Zanaflex and either fluvoxamine or ciprofloxacin is most likely due to inhibition of CYP1A2 by fluvoxamine or ciprofloxacin. The effect of fluvoxamine on the pharmacokinetics of a single 4 mg dose of Zanaflex was studied in 10 healthy subjects. The Cmax, AUC, and half-life of tizanidine increased by 12-fold, 33-fold, and 3-fold, respectively. The effect of ciprofloxacin on the pharmacokinetics of a single 4 mg dose of Zanaflex was studied in 10 healthy subjects. The Cmaxand AUC of tizanidine increased by 7-fold and 10-fold, respectively [see Contraindications (4)] .

Although there have been no clinical studies evaluating the effects of other CYP1A2 inhibitors on tizanidine, other CYP1A2 inhibitors, such as zileuton, other fluoroquinolones, antiarrhythmics (amiodarone, mexiletine, propafenone and verapamil), cimetidine, famotidine, oral contraceptives, acyclovir and ticlopidine, may also lead to substantial increases in tizanidine blood concentrations [see Warnings and Precautions (5.5)] .

In vitro studies of cytochrome P450 isoenzymes using human liver microsomes indicate that neither tizanidine nor the major metabolites are likely to affect the metabolism of other drugs metabolized by cytochrome P450 isoenzymes.

Oral Contraceptives

No specific pharmacokinetic study was conducted to investigate interaction between oral contraceptives and Zanaflex. Retrospective analysis of population pharmacokinetic data following single and multiple dose administration of 4 mg Zanaflex, however, showed that women concurrently taking oral contraceptives had 50% lower clearance of tizanidine compared to women not on oral contraceptives [see Warnings and Precautions (5.5)] .

Acetaminophen

Tizanidine delayed the Tmaxof acetaminophen by 16 minutes. Acetaminophen did not affect the pharmacokinetics of tizanidine.

Alcohol

Alcohol increased the AUC of tizanidine by approximately 20%, while also increasing its Cmaxby approximately 15%. This was associated with an increase in side effects of tizanidine. The CNS depressant effects of tizanidine and alcohol are additive.

13 NONCLINICAL TOXICOLOGY

13.1 Carcinogenesis, Mutagenesis, Impairment of Fertility

Carcinogenesis

Tizanidine was administered to mice for 78 weeks at oral doses up to 16 mg/kg/day, which is 2 times the maximum recommended human dose (MRHD) of 36 mg/day on a body surface area (mg/m^2) basis. Tizanidine was administered to rats for 104 weeks at oral doses up to 9 mg/kg/day, which is 2.5 times the MRHD on a mg/m^2basis. There was no increase in tumors in either species.

Mutagenesis

Tizanidine was negative in in vitro(bacterial reverse mutation [Ames], mammalian gene mutation, and chromosomal aberration test in mammalian cells) and in vivo(bone marrow micronucleus, and cytogenetics) assay.

Impairment of Fertility

Oral administration of tizanidine to rats prior to and during mating and continuing during early pregnancy in females resulted in reduced fertility in male and female rats at doses of 30 and 10 mg/kg/day, respectively. No effect on fertility was observed at doses of 10 (male) and 3 (female) mg/kg/day, which are approximately 3 times and similar to the MRHD, respectively, on a mg/m^2basis.

14 CLINICAL STUDIES

Tizanidine’s capacity to reduce increased muscle tone associated with spasticity was demonstrated in two adequate and well controlled studies in patients with multiple sclerosis or spinal cord injury (Studies 1 and 2).

Single-Dose Study in Patients with Multiple Sclerosis with Spasticity

In Study 1, patients with multiple sclerosis were randomized to receive single oral doses of drug or placebo. Patients and assessors were blind to treatment assignment and efforts were made to reduce the likelihood that assessors would become aware indirectly of treatment assignment (e.g., they did not provide direct care to patients and were prohibited from asking questions about side effects). In all, 140 patients received placebo, 8 mg or 16 mg of Zanaflex.

Response was assessed by physical examination; muscle tone was rated on a 5 point scale (Ashworth score), with a score of 0 used to describe normal muscle tone. A score of 1 indicated a slight spastic catch while a score of 2 indicated more marked muscle resistance. A score of 3 was used to describe considerable increase in tone, making passive movement difficult. A muscle immobilized by spasticity was given a score of 4. Spasm counts were also collected.

Assessments were made at 1, 2, 3 and 6 hours after treatment. A statistically significant reduction of the Ashworth score for Zanaflex compared to placebo was detected at 1, 2 and 3 hours after treatment. Figure 2below shows a comparison of the mean change in muscle tone from baseline as measured by the Ashworth scale. The greatest reduction in muscle tone was 1 to 2 hours after treatment. By 6 hours after treatment, muscle tone in the 8 and 16 mg Zanaflex groups was indistinguishable from muscle tone in placebo treated patients. Within a given patient, improvement in muscle tone was correlated with plasma concentration. Plasma concentrations were variable from patient to patient at a given dose. Although 16 mg produced a larger effect, adverse events including hypotension were more common and more severe than in the 8 mg group. There were no differences in the number of spasms occurring in each group.

Seven-Week Study in Patients with Spinal Cord Injury with Spasticity

In a 7-week study (Study 2), 118 patients with spasticity secondary to spinal cord injury were randomized to either placebo or Zanaflex. Steps similar to those taken in the first study were employed to ensure the integrity of blinding.

Patients were titrated over 3 weeks up to a maximum tolerated dose or 36 mg daily given in three unequal doses (e.g., 10 mg given in the morning and afternoon and 16 mg given at night). Patients were then maintained on their maximally tolerated dose for 4 additional weeks (i.e., maintenance phase). Throughout the maintenance phase, muscle tone was assessed on the Ashworth scale within a period of 2.5 hours following either the morning or afternoon dose. The number of daytime spasms was recorded daily by patients.

At endpoint (the protocol-specified time of outcome assessment), there was a statistically significant reduction in muscle tone and frequency of spasms in the Zanaflex treated group compared to placebo. The reduction in muscle tone was not associated with a reduction in muscle strength (a desirable outcome) but also did not lead to any consistent advantage of Zanaflex treated patients on measures of activities of daily living. Figure 3below shows a comparison of the mean change in muscle tone from baseline as measured by the Ashworth scale.

16 HOW SUPPLIED/STORAGE AND HANDLING

16.1 Zanaflex Capsules®

Zanaflex Capsules®(tizanidine hydrochloride) capsules are available in three strengths as two-piece hard gelatin capsules containing tizanidine hydrochloride 2.29 mg, 4.58 mg and 6.87 mg, equivalent to 2 mg, 4 mg and 6 mg tizanidine base.

- The 2 mg capsules have a light blue opaque body with a light blue opaque cap with “2 MG” printed on the cap: bottles of 150 capsules (NDC 70515-602-15)
- The 4 mg capsules have a white opaque body with a blue opaque cap with “4 MG” printed on the cap: bottles of 150 capsules (NDC 70515-604-15)
- The 6 mg capsules have a blue opaque body with a white stripe and blue opaque cap with “6 MG” printed on the capsules: bottles of 150 capsules (NDC 70515-606-15)

Store at 25°C (77°F); excursions permitted to 15°C to 30°C (59°F to 86°F) [see USP Controlled Room Temperature]. Dispense in containers with child resistant closure.

16.2 Zanaflex® Tablets

Zanaflex®(tizanidine hydrochloride) tablets are available as 4 mg white, uncoated tablets containing tizanidine hydrochloride 4.58 mg, equivalent to 4 mg tizanidine base. The tablets have a quadrisecting score on one side and are debossed with “A594” on the other side. Tablets are provided as follows: bottles of 150 tablets (NDC 70515-594-15).

Store at 25°C (77°F); excursions permitted to 15°C to 30°C (59°F to 86°F) [see USP Controlled Room Temperature].

Dispense in containers with child resistant closure.

17 PATIENT COUNSELING INFORMATION

Serious Drug Interactions

Advise patients they should not take Zanaflex if they are taking fluvoxamine or ciprofloxacin because of the increased risk of serious adverse reactions including severe lowering of blood pressure and sedation. Instruct patients to inform their physicians or pharmacists when they start or stop taking any medication because of the risks associated with interaction between Zanaflex and other medicines.

Zanaflex Dosing

Tell patients to take Zanaflex exactly as prescribed (consistently either with or without food) and not to switch between tablets and capsules. Inform patients that they should not take more Zanaflex than prescribed because of the risk of adverse events at single doses greater than 8 mg or total daily doses greater than 36 mg. Tell patients that they should not suddenly discontinue Zanaflex, because rebound hypertension and tachycardia may occur.

Effects of Zanaflex

Warn patients that they may experience hypotension and to be careful when changing from a lying or sitting to a standing position. Tell patients that Zanaflex may cause them to become sedated or somnolent and they should be careful when performing activities that require alertness, such as driving a vehicle or operating machinery. Tell patients that the sedation may be additive when Zanaflex is taken in conjunction with drugs (baclofen, benzodiazepines) or substances (e.g., alcohol) that act as CNS depressants. Remind patients that if they depend on their spasticity to sustain posture and balance in locomotion, or whenever spasticity is utilized to obtain increased function, that Zanaflex decreases spasticity and caution should be used.

Zanaflex®capsules is a registered trademark of Covis Pharma. Zanaflex®tablets is a registered trademark of Covis Pharma.

Manufactured for:
Covis Pharma
Zug, 6300 Switzerland

©2020 Covis Pharma, All rights reserved.

PRINCIPAL DISPLAY PANEL - 2 mg Capsule Bottle

NDC 70515-602-15

Rx only

Zana flex
Capsules®
(tizanidine hydrochloride)

2 mg

150 Capsules

STOP
Not interchangeable
with tizanidine tablets
or Zanaflex®tablets.

Each capsule
contains 2.29 mg
tizanidine
hydrochloride,
equivalent to 2 mg
tizanidine base.

COVIS
Manufactured for:
Covis Pharma
Zug, 6300 Switzerland

100337
Rev. 5/18

Refer to package insert for
prescribing information.

Store at 25°C (77°F); excursions
permitted to 15-30°C (59-86°F)
[see USP Controlled Room
Temperature].

Dispense in containers with
child resistant closure.

KEEP THIS AND ALL
MEDICATION OUT OF
REACH OF CHILDREN.

020602

LOT
123ABC2D
EXP
MMMYYYY

SN12345678901234
GTIN 00370515602151

PRINCIPAL DISPLAY PANEL - 4 mg Capsule Bottle

NDC 70515-604-15

Rx only

Zana flex
Capsules®
(tizanidine hydrochloride)

4 mg

150 Capsules

STOP
Not interchangeable
with tizanidine tablets
or Zanaflex®tablets.

Each capsule
contains 4.58 mg
tizanidine
hydrochloride,
equivalent to 4 mg
tizanidine base.

COVIS
Manufactured for:
Covis Pharma
Zug, 6300 Switzerland

100338
Rev. 5/18

Refer to package insert for
prescribing information.

Store at 25°C (77°F); excursions
permitted to 15-30°C (59-86°F)
[see USP Controlled Room
Temperature].

Dispense in containers with
child resistant closure.

KEEP THIS AND ALL
MEDICATION OUT OF
REACH OF CHILDREN.

020601

LOT
123ABC2D
EXP
MMMYYYY

SN 12345678901234
GTIN 00370515604155

PRINCIPAL DISPLAY PANEL - 6 mg Capsule Bottle

NDC 70515-606-15

Rx only

Zana flex
Capsules®
(tizanidine hydrochloride)

6 mg

150 Capsules

STOP
Not interchangeable
with tizanidine tablets
or Zanaflex®tablets.

Each capsule
contains 6.87 mg
tizanidine
hydrochloride,
equivalent to 6 mg
tizanidine base.

COVIS
Manufactured for:
Covis Pharma
Zug, 6300 Switzerland

100339
Rev. 5/18

Refer to package insert for
prescribing information.

Store at 25°C (77°F); excursions
permitted to 15-30°C (59-86°F)
[see USP Controlled Room
Temperature].

Dispense in containers with
child resistant closure.

KEEP THIS AND ALL
MEDICATION OUT OF
REACH OF CHILDREN.

020600

LOT
123ABC2D
EXP
MMMYYYY

SN 12345678901234
GTIN 00370515606159

PRINCIPAL DISPLAY PANEL - 4 mg Tablet Bottle

NDC 70515-594-15

Zanaflex®
(tizanidine hydrochloride)

4 mg

150 Tablets

STOP
Zanaflex®(tizanidine hydrochloride)
tablets are not interchangeable
with Zanaflex Capsules®.

Each tablet contains 4.576 mg tizanidine HCl
equivalent to 4 mg tizanidine base.

COVIS
Manufactured for:
Covis Pharma
Zug, 6300 Switzerland

100335
Rev. 5/18

Refer to package insert for
prescribing information.

Rx only

Store at 25°C (77°F); excursions permitted
to 15-30°C (59-86°F) [see USP Controlled
Room Temperature]. Dispense in containers
with child resistant closure.

KEEP THIS AND ALL MEDICATION OUT
OF REACH OF CHILDREN.